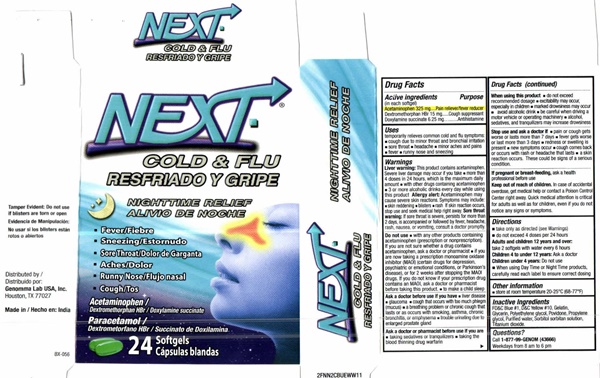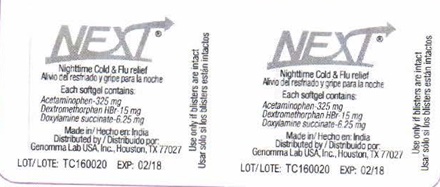 DRUG LABEL: NEXT COLD and FLU
NDC: 50066-603 | Form: CAPSULE, GELATIN COATED
Manufacturer: Genomma Lab USA, Inc.
Category: otc | Type: HUMAN OTC DRUG LABEL
Date: 20170421

ACTIVE INGREDIENTS: ACETAMINOPHEN 325 mg/1 1; DEXTROMETHORPHAN HYDROBROMIDE 15 mg/1 1; DOXYLAMINE SUCCINATE 6.25 mg/1 1
INACTIVE INGREDIENTS: FD&C BLUE NO. 1; D&C YELLOW NO. 10; GELATIN; GLYCERIN; POLYETHYLENE GLYCOL 400; POVIDONE; PROPYLENE GLYCOL; WATER; SORBITOL; TITANIUM DIOXIDE

NEXT Nighttime Cold & Flu - 603

Drug Facts Active ingredients (in each softgel)

Acetaminophen 325 mg
Dextromethorphan HBr 15 mg
Doxylamine succinate 6.25 mg

Purpose

Pain reliever/fever reducer
Cough suppressant
Antihistamine

Uses

temporarily relieves common cold and flu symptoms:

- cough due to minor throat and bronchial irritation
- sore throat
- headache
- minor aches and pains
- fever
- runny nose and sneezing

Warnings

Liver warning: This product cantains acetaminophen. Severe liver damage may occur if you take

- more than 4 doses in 24 hours, which is the maxium daily amount
- with other drugs containing acetaminophen
- 3 or more alcoholic drinks daily while using this product

Allergy alert: Acetaminophen may cause severe skin reactions. Symptoms may include:

- skin reddening
- blisters
- rash

If skin reaction occurs, stop use and seek medical help right away.

Sore throat warning: If sore throat is severe, persists more than 2 days, is accompanied or followed by fever, headache, rash, nausea or vomiting, consult a doctor promptly.

Do not use

- with any other drug containing acetaminophen (prescription or nonprescription). If you are not sure whether a drug contains acetaminophen, ask a doctor or pharmacist
- if you are now taking a prescription monoamine oxidase inhibitor (MAOI) (certain drugs for depression, psychiatric, or emotional conditions, or Parkinson's disease), or for 2 weeks after stopping an MAOI drug. If you do not know if ask a doctor or pharmacist before taking this product.
- to make a child sleep

Ask a doctor before use if you have

- liver disease
- glaucoma
- cough that occurs with too much phlegm (mucus)
- a breathing problem or chronic cough that lasts or as occurs with smoking, asthma, chronic bronchitis, or emphysema
- trouble urinating due to enlarged prostate gland

Ask a doctor or pharmacist before use if you are

- taking sedatives or tranquilizers
- taking the blood thinning drug warfarin

When using this product

- do not exceed recommended dosage
- excitability may occur, especially in children
- marked drowsiness may occur
- avoid alcoholic drink
- be careful when driving a motor vehicle or operating machinery
- alcohol, sedatives, and tranquilizers may increase drowsiness

Stop use and ask a doctor if

- pain or cough gets worse or lasts more than 7 days
- fever gets worse or lasts more than 3 days
- redness or swelling is present
- new symptoms occur
- cough comes back or occurs with rash or headache that lasts
- a skin reaction occurs. These could be signs of a serious condition.

If pregnant or breast-feeding,

ask a health professional before use

Keep out of reach of children. In case of accidental overdose, get medical help or contact a Poison Control Center right away. Quick medical attention is critical for adults as well as for children, even if you do not notice any signs or symptoms.

Directions

- take only as directed (see Warnings)
- do not exceed 4 doses per 24 hours
- Adults and children 12 years and over:
  take 2 softgels with water every 6 hours
- Children 4 to under 12 years: Ask a doctor

Children under 4 years: Do not use

- When using Day Time ot Night Time products, carefully read each label to ensure correct dosing

Other information

- store at room temperature 20-25°C (68-77°F)

Inactive Ingredients

FD&C Blue # 1, D&C Yellow # 10, Gelatin, Glycerin, Polyethylene glycol, Povvidone, Propylene glycol, Purified water, Sorbital sorbitan solution, Titanium dioxide.

Questions?

Call 1-877-99-Genom (43666)
Weekdays from 8am to 6 pm

NEXT COLD & FLU NIGHTTIME product label

NEXT
COLD & FLU

NIGHTTIME RELIEF

- Fever
- Sneezing
- Sore Throat
- Aches
- Runny Nose
- Cough

Acetaminophen/
Dextromethorphan HBr / Doxylamine succinate

Tamper evident: Do not use if blisters are torn or open

Distributed by:
Genomma Lab USA, Inc.
Houston, TX 77027

Made in India

BX-056